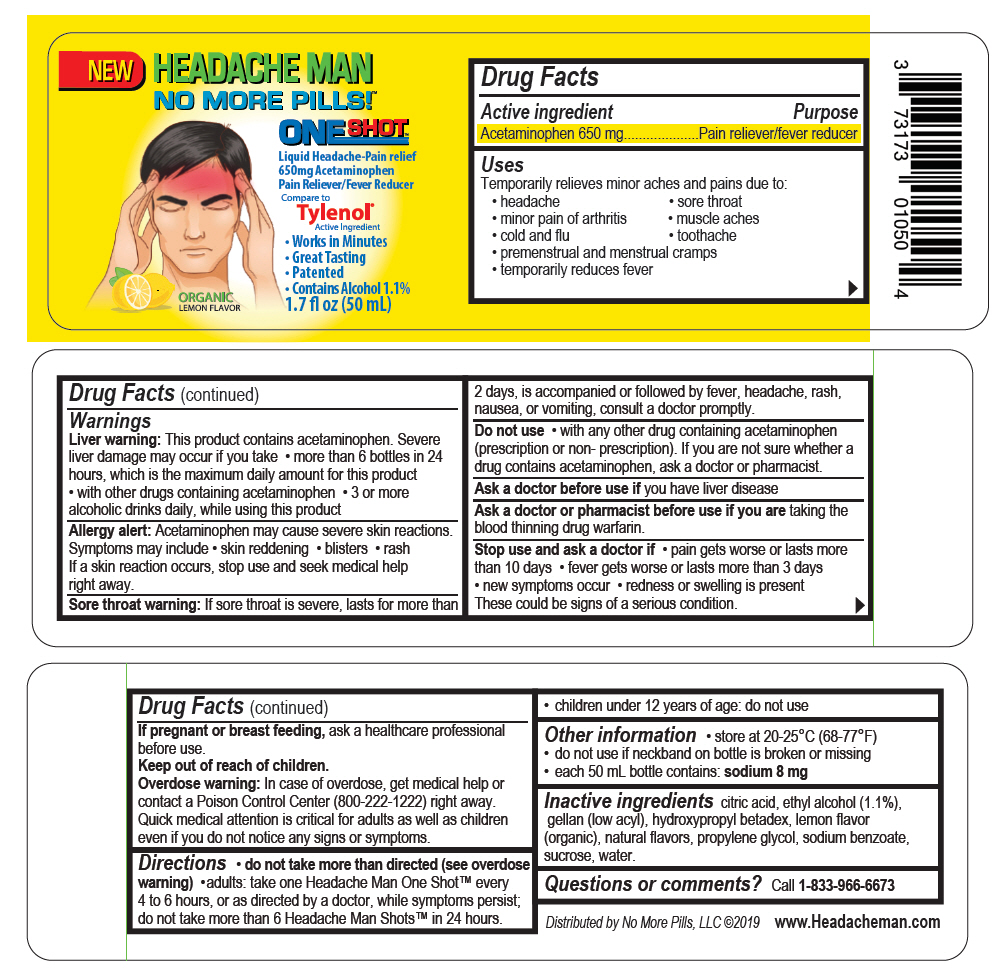 DRUG LABEL: Headache Man 
NDC: 73173-010 | Form: LIQUID
Manufacturer: No More Pills, LLC
Category: otc | Type: HUMAN OTC DRUG LABEL
Date: 20201208

ACTIVE INGREDIENTS: Acetaminophen 650 mg/50 mL
INACTIVE INGREDIENTS: ANHYDROUS CITRIC ACID; ALCOHOL; Gellan Gum (Low Acyl); Hydroxypropyl Betadex; Propylene Glycol; Sodium Benzoate; Sucrose; Water

Headache Man
No More Pills!™, One Shot™, Liquid Headache Pain Relief

Drug Facts

Active Ingredient

Acetaminophen 650mg

Purpose

Pain reliever/fever reducer

Uses

Temporarily relieves minor aches and pains due to:

- headache
- sore throat
- minor pain of arthritis
- muscle aches
- cold and flu
- toothache
- premenstrual and menstrual cramps
- temporarily reduces fever

Warnings

Liver warning

This product contains acetaminophen. Severe liver damage may occur if you take

- more than 6 bottles in 24 hours, which is the maximum daily amount for this product
- with other drugs containing acetaminophen
- 3 or more alcoholic drinks daily, while using this product

Allergy alert

Acetaminophen may cause severe skin reactions.

Symptoms may include

- skin reddening
- blisters
- rash

If a skin reaction occurs, stop use and seek medical help right away.

Sore throat warning

If sore throat is severe, lasts for more than 2 days, is accompanied or followed by fever, headache, rash, nausea, or vomiting, consult a doctor promptly.

Do not use

- with any other drug containing acetaminophen (prescription or non- prescription). If you are not sure whether a drug contains acetaminophen, ask a doctor or pharmacist.

Ask a doctor before use if you have liver disease

Ask a doctor or pharmacist before use if you are taking the blood thinning drug warfarin.

Stop use and ask a doctor if

- pain gets worse or lasts more than 10 days
- fever gets worse or lasts more than 3 days
- new symptoms occur
- redness or swelling is present

These could be signs of a serious condition.

PREGNANCY OR BREAST FEEDING

If pregnant or breast feeding, ask a healthcare professional before use.

Keep out of reach of children.

Overdose warning

In case of overdose, get medical help or contact a Poison Control Center (800-222-1222) right away. Quick medical attention is critical for adults as well as children even if you do not notice any signs or symptoms.

Directions

- do not take more than directed (see overdose warning)
- adults: take one Headache Man One Shot™ every 4 to 6 hours, or as directed by a doctor, while symptoms persist; do not take more than 6 Headache Man Shots™ in 24 hours.
- children under 12 years of age: do not use

Other information

- store at 20-25°C (68-77°F)
- do not use if neckband on bottle is broken or missing
- each 50 mL bottle contains: sodium 8 mg

Inactive ingredients

citric acid, ethyl alcohol (1.1%), gellan (low acyl), hydroxypropyl betadex, lemon flavor (organic), natural flavors, propylene glycol, sodium benzoate, sucrose, water.

Questions or comments?

Call 1-833-966-6673

Distributed by No More Pills, LLC

PRINCIPAL DISPLAY PANEL - 50 mL Bottle Label

NEW

HEADACHE MAN
NO MORE PILLS!™

ONE SHOT™

Liquid Headache-Pain relief
650mg Acetaminophen
Pain Reliever/Fever Reducer
Compare to
Tylenol®
Active Ingredient

- Works in Minutes
- Great Tasting
- Patented
- Contains Alcohol 1.1%

ORGANIC
LEMON FLAVOR

1.7 fl oz (50 mL)